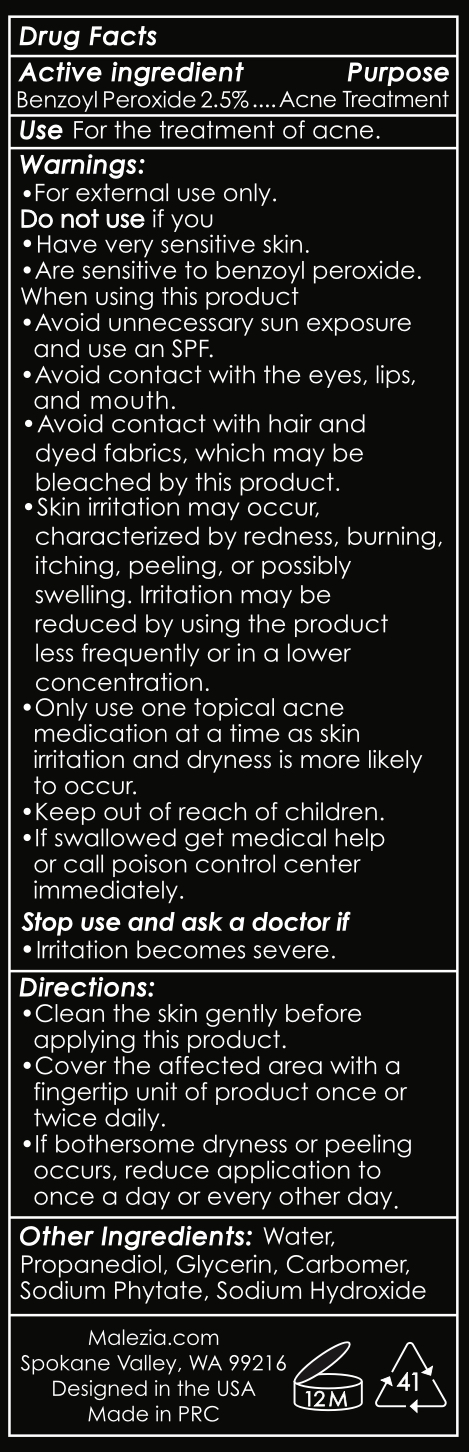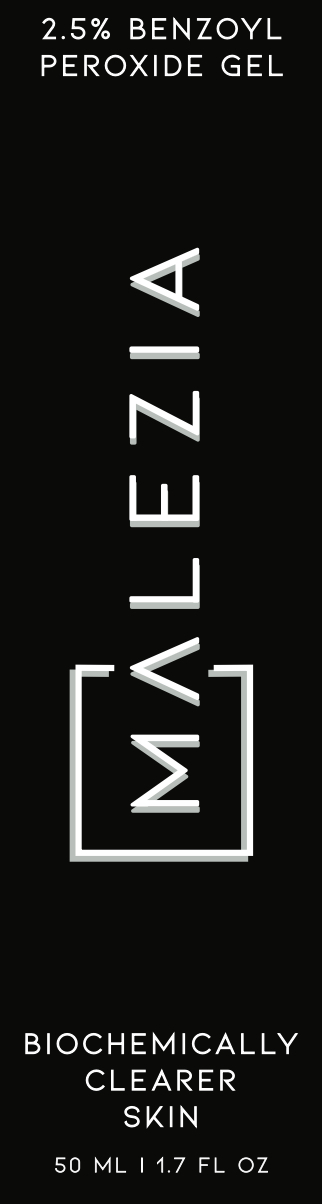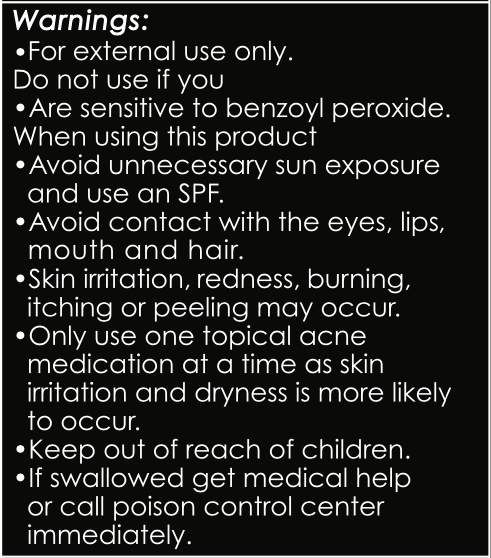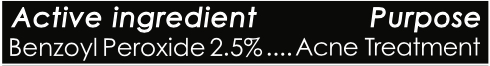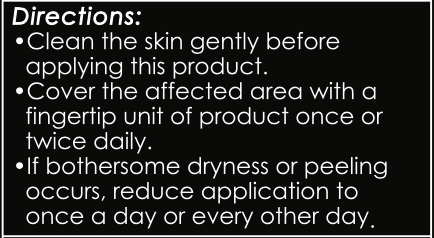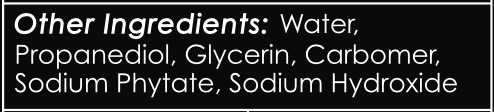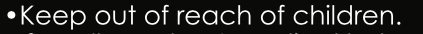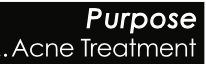 DRUG LABEL: Benzoyl Peroxide
NDC: 77924-002 | Form: GEL
Manufacturer: Malezia LLC
Category: otc | Type: HUMAN OTC DRUG LABEL
Date: 20241030

ACTIVE INGREDIENTS: BENZOYL PEROXIDE 25 mg/1000 mg
INACTIVE INGREDIENTS: GLYCERIN; SODIUM HYDROXIDE; WATER; CARBOMER 980; PHYTATE SODIUM; PROPANEDIOL

Benzoyl Peroxide

PACKAGE LABEL

50 mL NDC: 77924-002-01

DOSAGE AND ADMINISTRATION

50 mL NDC: 77924-002-01

WARNINGS

50 mL NDC: 77924-002-01

INACTIVE INGREDIENT

50 mL NDC: 77924-002-01

ACTIVE INGREDIENT

50 mL NDC: 77924-002-01

PURPOSE

50 mL NDC: 77924-002-01

INDICATIONS AND USAGE

50 mL NDC: 77924-002-01

KEEP OUT OF REACH OF CHILDREN

50 mL NDC: 77924-002-01